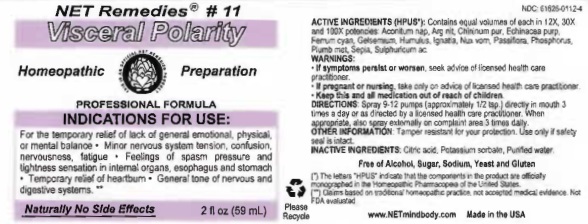 DRUG LABEL: Visceral Polarity
NDC: 61626-0112 | Form: LIQUID
Manufacturer: NET Remedies
Category: homeopathic | Type: HUMAN PRESCRIPTION DRUG LABEL
Date: 20210121

ACTIVE INGREDIENTS: ACONITUM NAPELLUS 12 [hp_X]/59 mL; SILVER NITRATE 12 [hp_X]/59 mL; QUININE 12 [hp_X]/59 mL; ECHINACEA PURPUREA 12 [hp_X]/59 mL; FERRIC FERROCYANIDE 12 [hp_X]/59 mL; GELSEMIUM SEMPERVIRENS ROOT 12 [hp_X]/59 mL; HOPS 12 [hp_X]/59 mL; STRYCHNOS IGNATII SEED 12 [hp_X]/59 mL; STRYCHNOS NUX-VOMICA SEED 12 [hp_X]/59 mL; PASSIFLORA INCARNATA FLOWERING TOP 12 [hp_X]/59 mL; PHOSPHORUS 12 [hp_X]/59 mL; LEAD 12 [hp_X]/59 mL; SEPIA OFFICINALIS JUICE 12 [hp_X]/59 mL; SULFURIC ACID 12 [hp_X]/59 mL
INACTIVE INGREDIENTS: CITRIC ACID MONOHYDRATE; POTASSIUM SORBATE; WATER

Visceral Polarity

ACTIVE INGREDIENT

ACTIVE INGREDIENTS (HPUS*): Contains equal volumes of each in 12X, 30X, and 100X potencies: Aconitum nap, Arg nit, Chininum pur, Echinscea purp, Ferrum cyan, Gelsenium, Humulus, Ignatia, Nux vom, Passiflora, Phorphorus, Plumb met, Sepia, Sulphuricum ac.

(*) The letters "HPUS" indicate that the components in the product are officially monographed in the Homeopathic Pharmacopeia of the United States.

(**) Claims based on traditonal homeopathic practice, not accepted medical evidence. Not FDA evaluated.

INDICATIONS AND USAGE

INDICATIONS FOR USE: For the temporary relief of lack of general emotional, physical, or mental balance • Minor nervous system tension, confusion, nervousness, fatigue • Feelings of spasm pressure and tightness sensation in internal organs, esophagus and stomach • Temporary relief of heartburn • General tone of nervous and digestive systems.**

WARNINGS:

• If symptoms persist or worsen, seek advice of licensed health care practitioner.

• If pregnant or nursing, take on only advice of licensed health care practitioner.

• Keep this and all medication out of reach of children.

KEEP OUT OF REACH OF CHILDREN

• Keep this and all medication out of reach of children.

DOSAGE AND ADMINISTRATION

DIRECTIONS: Spray 9-12 pumps (approximately 1/2 tsp.) directly in mouth 3 times a day or as directed by a licensed health care practitioner. When appropriate, also spray externally on complaint area 3 times daily.

OTHER INFORMATION: Tamper resistant for your protection. Use only if safety seal is intact.

INACTIVE INGREDIENTS: Citric acid, Potassium sorbabte, Purifed water .

Free of Alcohol, Sugar, Sodium, Yeast and Gluten

QUESTIONS

www.NETmindbody.com

Made in the USA.

PACKAGE LABEL

NET Remedies #11

Visceral Polarity

Homeopathic Preparation

PROFESSIONAL FORMULA

Naturally No Side Effects

2 fl oz (59 mL)

PURPOSE

INDICATIONS FOR USE: For the temporary relief of lack of general emotional, physical, or mental balance • Minor nervous system tension, confusion, nervousness, fatigue • Feelings of spasm pressure and tightness sensation in internal organs, esophagus and stomach • Temporary relief of heartburn • General tone of nervous and digestive systems.**